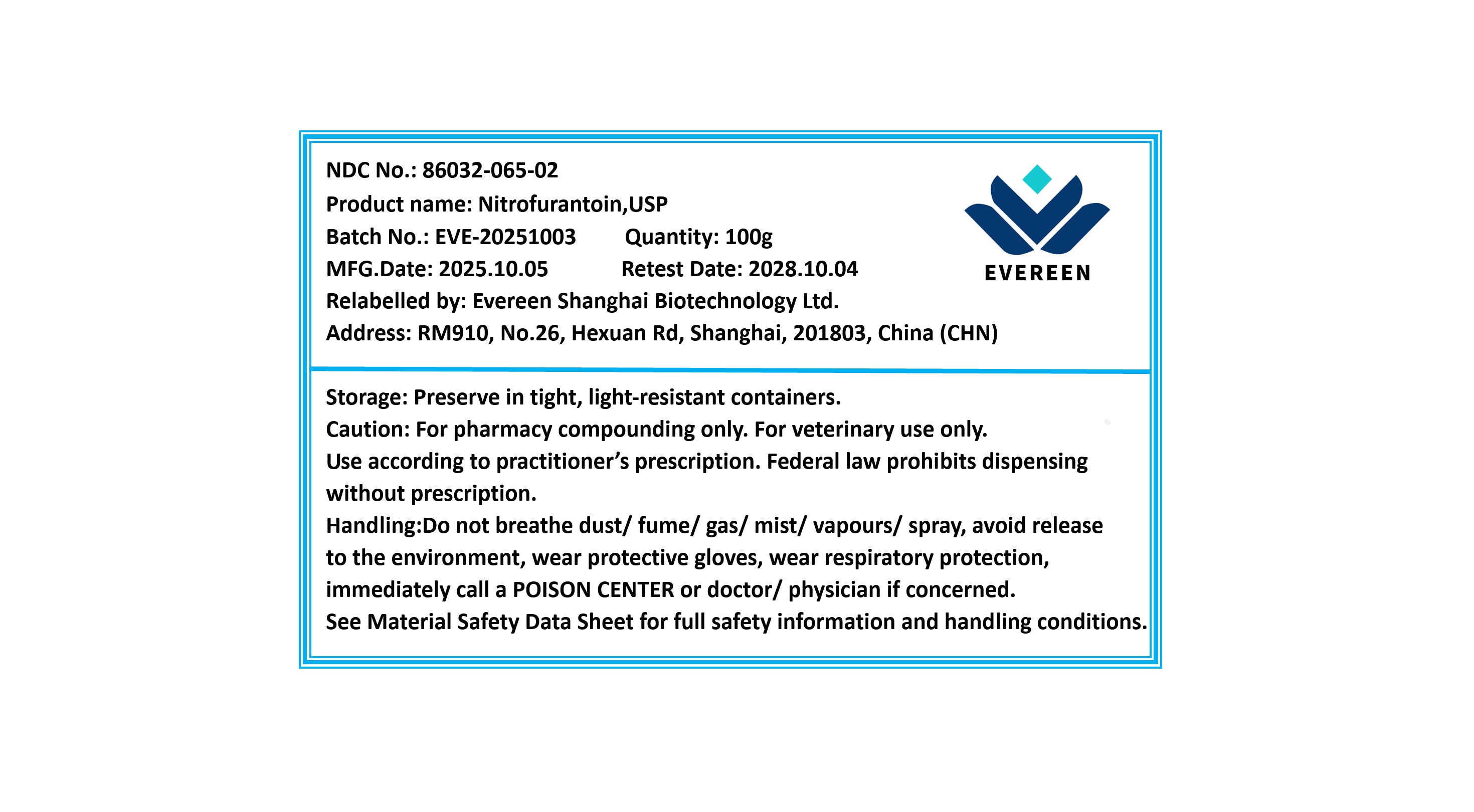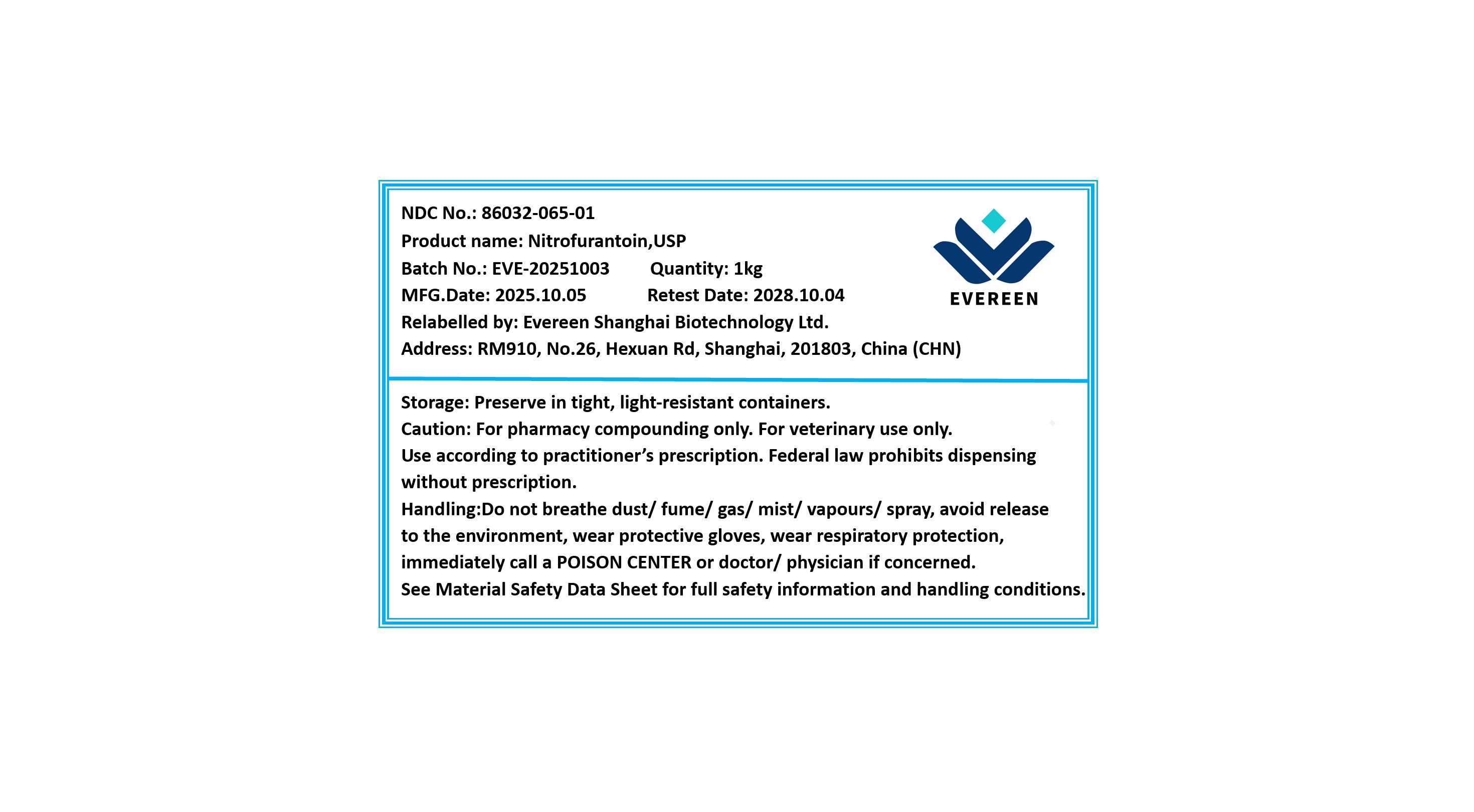 DRUG LABEL: Nitrofurantoin
NDC: 86032-065 | Form: POWDER
Manufacturer: Evereen Shanghai Biotechnology Ltd.
Category: other | Type: BULK INGREDIENT - ANIMAL DRUG
Date: 20251217

ACTIVE INGREDIENTS: NITROFURANTOIN 1 kg/1 kg

Nitrofurantoin